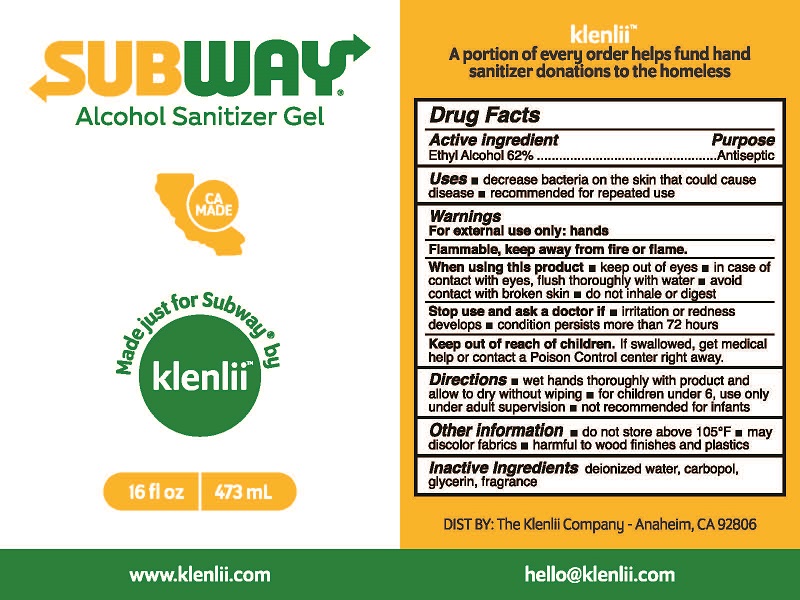 DRUG LABEL: SUBWAY ALCOHOL SANITIZER
NDC: 78016-103 | Form: GEL
Manufacturer: Klenlii Company
Category: otc | Type: HUMAN OTC DRUG LABEL
Date: 20240509

ACTIVE INGREDIENTS: ALCOHOL 62 mL/100 mL
INACTIVE INGREDIENTS: WATER; CARBOMER HOMOPOLYMER, UNSPECIFIED TYPE; GLYCERIN

KLENLII SUBWAY ALCOHOL SANITIZER GEL (62% ETHYL ALCOHOL) (78016-103)

ACTIVE INGREDIENT

ETHYL ALCOHOL 62%

PURPOSE

ANTISEPTIC

USES

- DECREASE BACTERIA ON SKIN THAT COULD CAUSE DISEASE
- RECOMMENDED FOR REPEATED USE

WARNINGS

FOR EXTERNAL USE ONLY: HANDS

FLAMMABLE, KEEP AWAY FROM FIRE OR FLAME.

WHEN USING THIS PRODUCT

- KEEP OUT OF EYES
- IN CASE OF CONTACT WITH EYES, FLUSH THOROUGHLY WITH WATER
- AVOID CONTACT WITH BROKEN SKIN
- DO NOT INHALE OR DIGEST

STOP USE AND ASK DOCTOR IF

- IRRITATION OR REDNESS DEVELOPS
- CONDITION PERSISTS MORE THAN 72 HOURS

KEEP OUT OF REACH OF CHILDREN. IF SWALLOWED, GET MEDICAL HELP OR CONTACT A POISON CONTROL CENTER RIGHT AWAY.

DIRECTIONS

- WET HANDS THOROUGHLY WITH PRODUCT AND ALLOW TO DRY WITHOUT WIPING
- NOT FOR CHILDREN UNDER 6, USE ONLY UNDER ADULT SUPERVISION
- NOT RECOMMENDED FOR INFANTS

INACTIVE INGREDIENTS

DEIONIZED WATER, CARBOPOL, GLYCERIN, FRAGRANCE